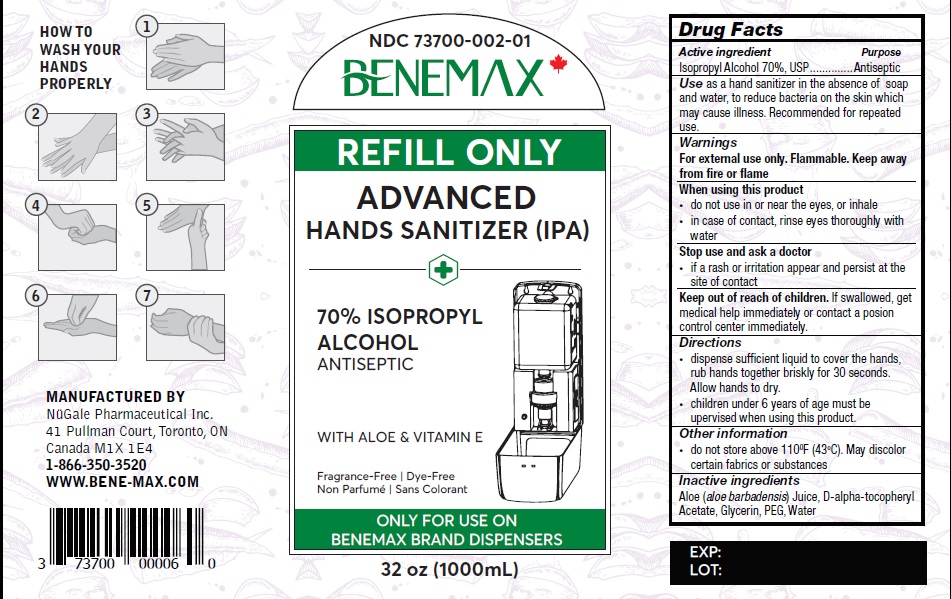 DRUG LABEL: BENEMAX ADVANCED Hand Sanitizer
NDC: 73700-002 | Form: LIQUID
Manufacturer: Nugale Pharmaceutical Inc
Category: otc | Type: HUMAN OTC DRUG LABEL
Date: 20211129

ACTIVE INGREDIENTS: ISOPROPYL ALCOHOL 70 mL/100 mL
INACTIVE INGREDIENTS: ALOE; .ALPHA.-TOCOPHEROL ACETATE, DL-; GLYCERIN; POLYETHYLENE GLYCOL, UNSPECIFIED; WATER

Drug Facts

Active ingredient

Isopropyl alcohol 70%, USP

Purpose

Antiseptic

Uses

as a hand sanitizer when there is no water, to reduce bacteria on the skin which can cause illness. Recommended for repeated use.

Warnings

Flammable, keep away from fire or flame

For external use only

When using this product

- do not use in or near the eyes, or inhale
- in case of contact, rinse eyes thoroughly with water

Stop use and ask a doctor

if a rash on irritation appear and remain at the site of contact

Keep out of reach of children.

If swallowed, get medical help right away or contact a Poison Control Center immediately.

Directions

- dispense sufficient liquid to cover the hands, rub hands together briskly for 30 seconds.

Allow hands to dry.

• children under 6 years of age must be upervised when using this product.

Other information

- do not store above 110^0F (43^0C). May discolor certain fabrics or substances

Inactive ingredient

Aloe (aloe barbadensis) Juice, D-alpha-tocopheryl Acetate, Glycerin, PEG, Water